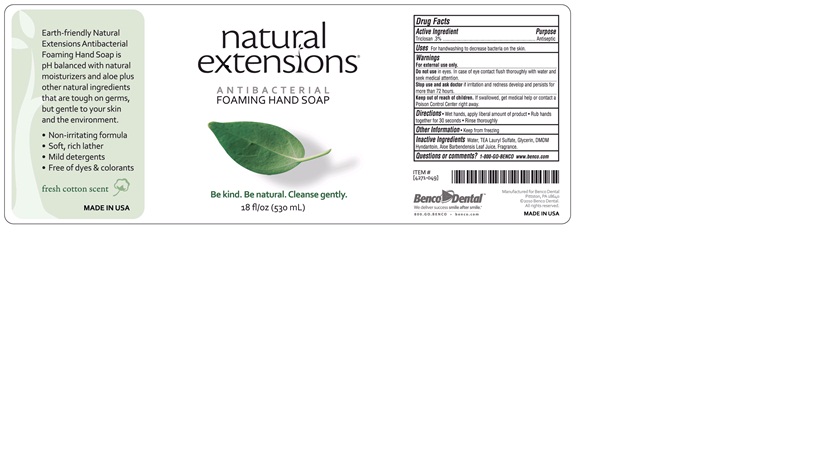 DRUG LABEL: natural extensions Antibacterial Foaming Hand Wash
NDC: 66975-103 | Form: SOAP
Manufacturer: Benco Dental Company
Category: otc | Type: HUMAN OTC DRUG LABEL
Date: 20120321

ACTIVE INGREDIENTS: TRICLOSAN 3 mL/1000 mL
INACTIVE INGREDIENTS: WATER; TROLAMINE LAURYL SULFATE; GLYCERIN; DMDM HYDANTOIN; ALOE VERA LEAF

natural extensions Antibacterial Foaming Hand Soap

Earth-friendly Natural Extensions Antibacterial Foaming Hand Soap is PH balanced with natural moisturizers and aloe plus other natural ingredients that are tough on germs, but gentle to your skin and the environment.
* Non-irritating formula
* Soft, rich lather
* Mild detergents
* Free of dyes and colorants

Active Ingredient

Triclosan .3%

Purpose

Antiseptic

Warnings

For external use only.

Do not use in eyes. In case of eye contact flush thoroughly with water and seek medical attention.

Stop use and ask doctor if irritation and redness develop and persists for more than 72 hours.

Keep out of reach of children. If swallowed, get medical help or contact a Poison Control Center right away.

Other Information

Keep from freezing

Inactive Ingredients

Water, TEA Lauryl Sulfate, Glycerin, DMDM Hydantoin, Aloe Barbadensis Leaf Juice, Fragrance.

Questions or comments? 1-800-GO-BENCO www.benco.com

Uses

For handwashing to decrease bacteria on the skin.

Directions

Wet hands and apply liberal amount of product. Rub hands together for 30 seconds. Rinse thoroughly.

PACKAGE LABEL

530 ml pump bottle